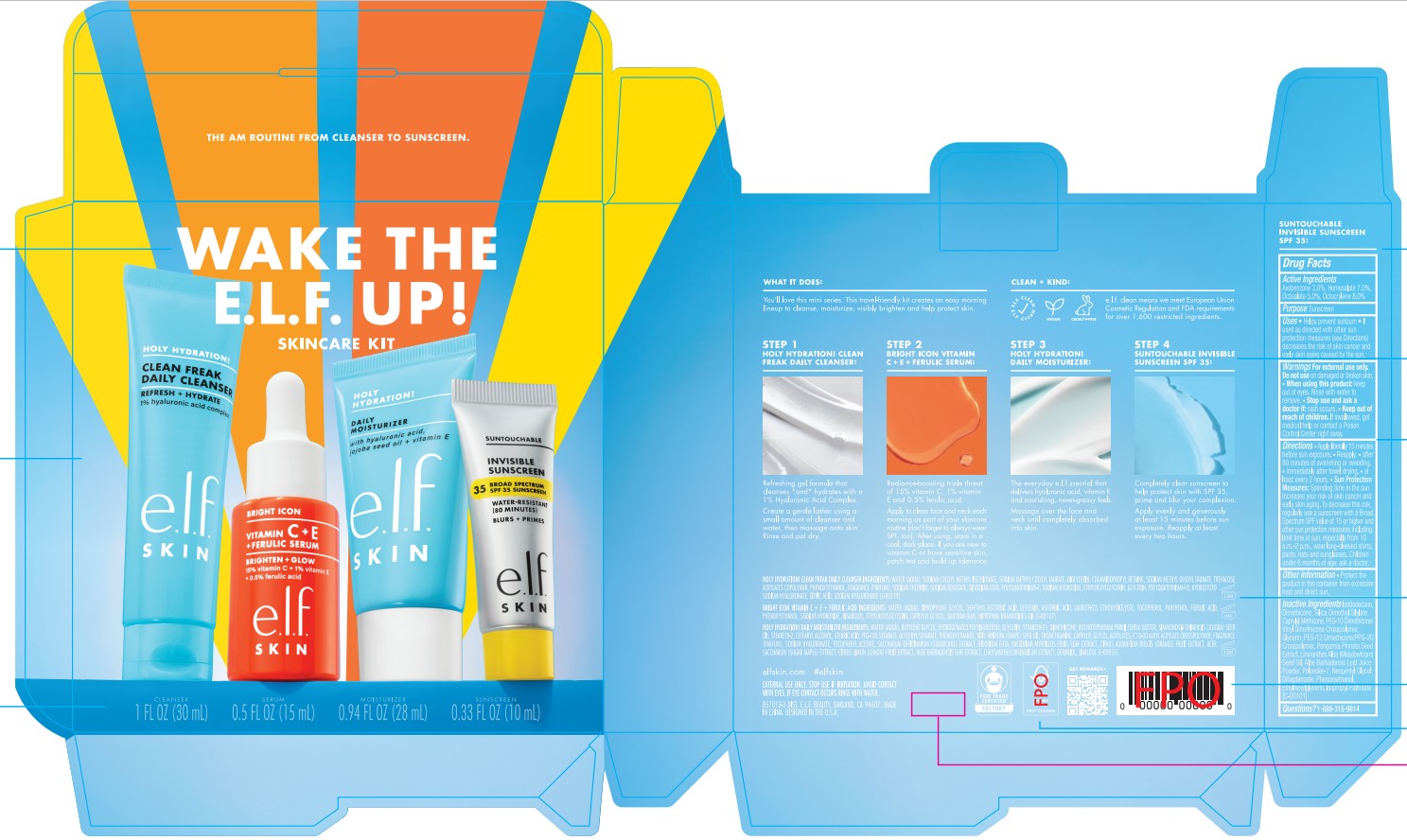 DRUG LABEL: e.l.f. Wake the E.L.F. Up Skincare Set
NDC: 76354-456 | Form: KIT | Route: TOPICAL
Manufacturer: e.l.f. Cosmetics, Inc
Category: otc | Type: HUMAN OTC DRUG LABEL
Date: 20260218

ACTIVE INGREDIENTS: HOMOSALATE 70 mg/1 mL; AVOBENZONE 30 mg/1 mL; OCTISALATE 50 mg/1 mL; OCTOCRYLENE 80 mg/1 mL
INACTIVE INGREDIENTS: CAPRYLYL METHICONE; PEG-12 DIMETHICONE/PPG-20 CROSSPOLYMER; POLYESTER-7; ETHYLHEXYLGLYCERIN; SILICA DIMETHYL SILYLATE; PHENOXYETHANOL; ISOPROPYL PALMITATE; ALOE BARBADENSIS LEAF POWDER; PONGAMIA PINNATA SEED; ISODODECANE; GLYCERIN; LIMNANTHES ALBA (MEADOWFOAM) SEED OIL; DIMETHICONE/VINYL DIMETHICONE CROSSPOLYMER (SOFT PARTICLE); DIMETHICONE; NEOPENTYL GLYCOL DIHEPTANOATE

e.l.f. Wake the E.L.F. Up Skincare Set

Active Ingredients

Avobenzone 3.0%

Homosalate 7.0%

Octisalate 5.0%

Octocrylene 8.0%

Purpose

Sunscreen

Uses

- Helps prevent sunburn
- If used as directed with other sun protection measures (see Directions) decreases the risk of skin cancer and early skin aging caused by the sun.

Warnings

For external use only.

Do not use

on damaged or broken skin.

When using this product:

- keep out of eyes. Rinse with water to remove.

Stop use and ask a doctor if:

- rash occurs.

Keep out of reach of children

- If swallowed, get medical help or contact a Poison Control Center right away.

Directions

- Apply generously and evenly 15 minutes before sun exposure.
- Reapply:
- after 80 minutes of swimming or sweating.
- immediately after towel drying.
- at least every 2 hours.
- Sun Protection Measures: Spending time in the sun increases your risk of skin cancer and early skin aging. To decrease this risk, regularly use a sunscreen with a Broad Spectrum SPF value of 15 or higher and other sun protection measures including:
- Limit time in sun, especially from 10 a.m.-2 p.m.
- Wear long-sleeved shirts, pants, hats and sunglasses.
- Children under 6 months: Ask a doctor.

Other Information

- Protect the product in this container from excessive heat and direct sun.

Inactive Ingredients

Isododecane, Dimethicone, Silica Dimethyl Silylate, Caprylyl Methicone, PEG-10 Dimethicone/Vinyl Dimethicone Crosspolymer, Glycerin, PEG-12 Dimethicone/PPG-20 Crosspolymer,Pongamia Pinnata Seed Extract, Limnanthes Alba (Meadowfoam) Seed Oil, Aloe Barbadensis Leaf Juice Powder, Polyester-7, Neopentyl Glycol Diheptanoate, Phenoxyethanol, Ethylhexylglycerin, Isopropyl Palmitate

Questions?

1-888-315-9814

Packaging Label

.